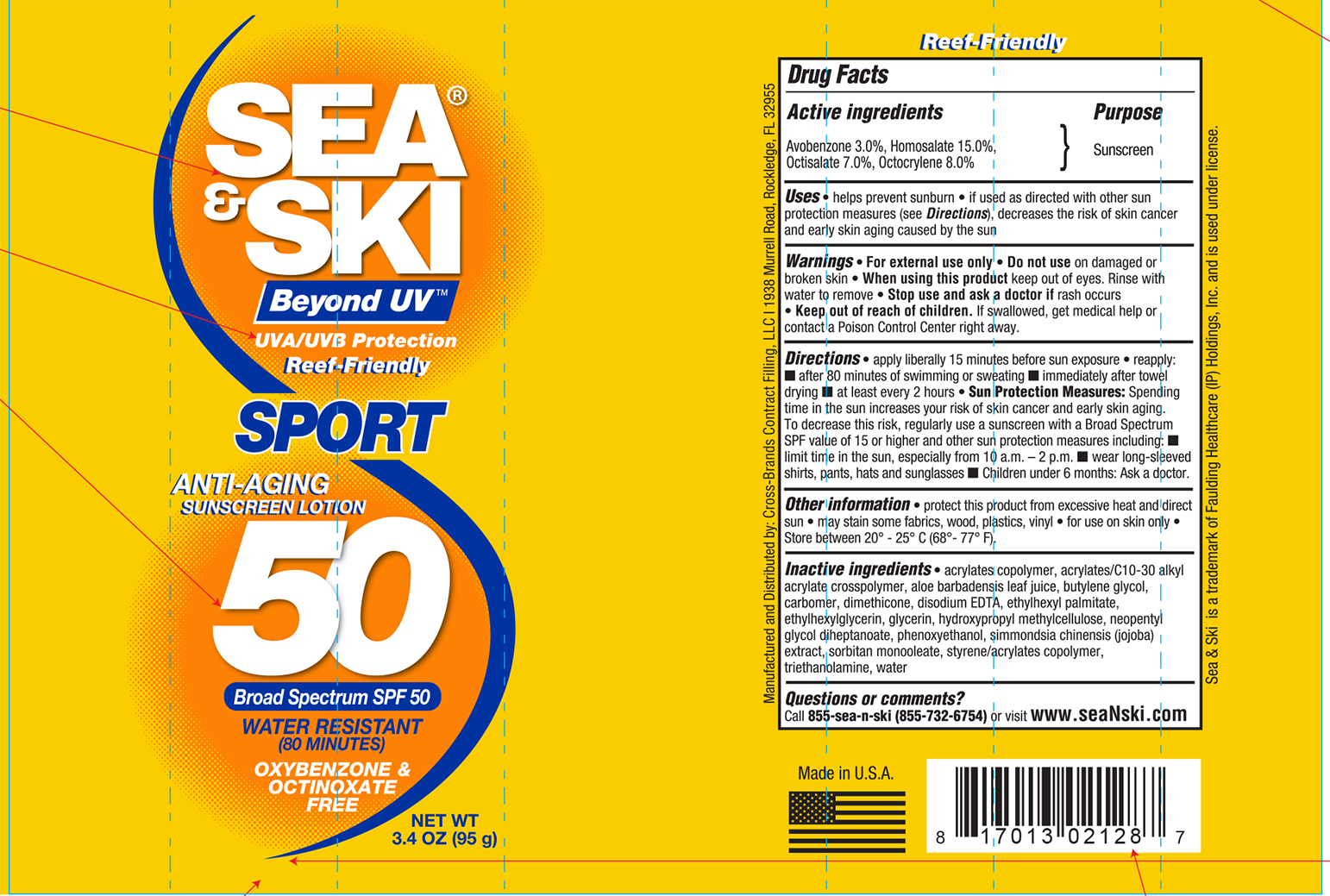 DRUG LABEL: Sea and Ski SPF 50 Sport
NDC: 73440-2128 | Form: LOTION
Manufacturer: Cross-Brands Contract Filling
Category: otc | Type: HUMAN OTC DRUG LABEL
Date: 20210219

ACTIVE INGREDIENTS: OCTISALATE 6.65 g/95 g; OCTOCRYLENE 7.6 g/95 g; AVOBENZONE 2.85 g/95 g; HOMOSALATE 14.25 g/95 g
INACTIVE INGREDIENTS: WATER 46.02 g/95 g

Sea&Ski SPF 50 Sport lotion 3.4oz